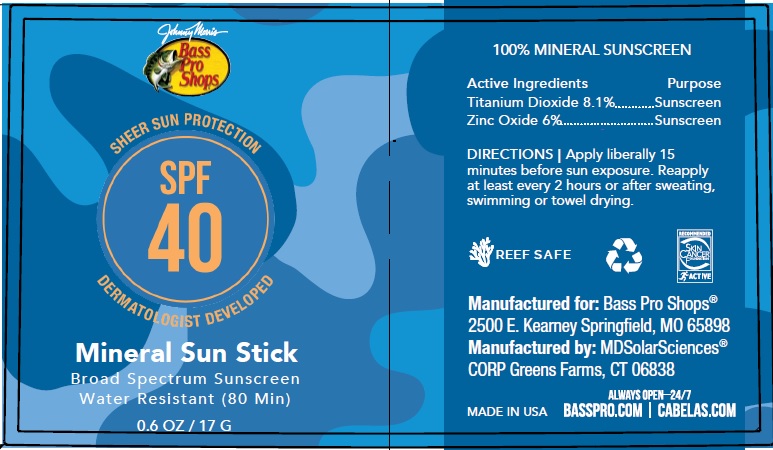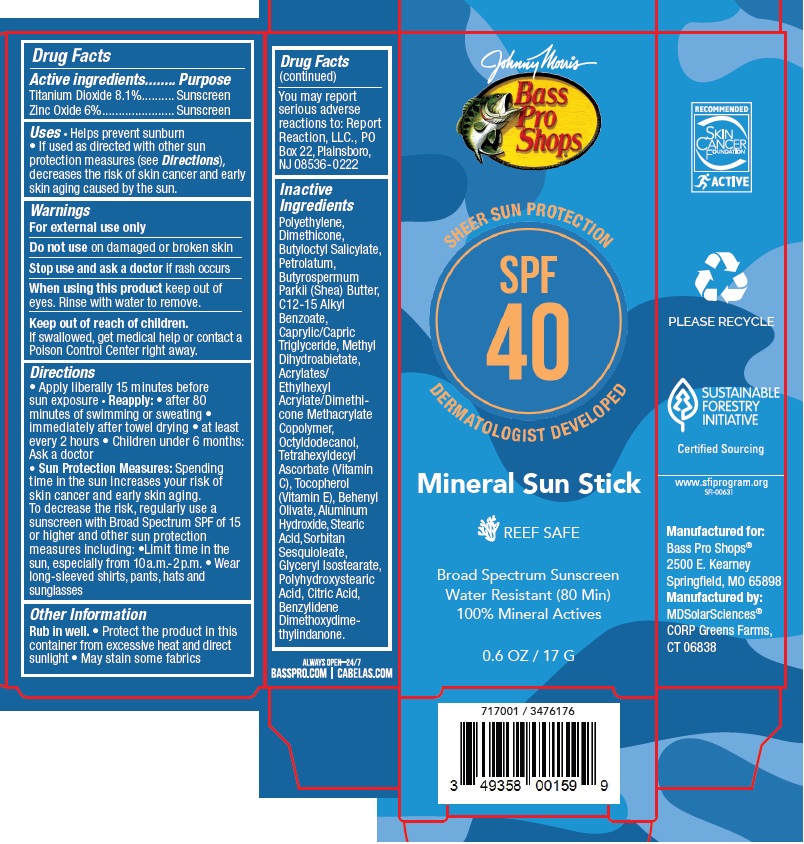 DRUG LABEL: Bass Pro Shops Mineral Sun Stick Sunscreen Broad Spec SPF 40
NDC: 14268-125 | Form: CREAM
Manufacturer: ENGLEWOOD LAB, INC.
Category: otc | Type: HUMAN OTC DRUG LABEL
Date: 20231212

ACTIVE INGREDIENTS: TITANIUM DIOXIDE 81 mg/1 g; ZINC OXIDE 60 mg/1 g
INACTIVE INGREDIENTS: HIGH DENSITY POLYETHYLENE; DIMETHICONE; BUTYLOCTYL SALICYLATE; PETROLATUM; SHEA BUTTER; ALKYL (C12-15) BENZOATE; METHYL DIHYDROABIETATE; OCTYLDODECANOL; TETRAHEXYLDECYL ASCORBATE; TOCOPHEROL; BEHENYL OLIVATE; ALUMINUM HYDROXIDE; STEARIC ACID; SORBITAN SESQUIOLEATE; GLYCERYL ISOSTEARATE; CITRIC ACID MONOHYDRATE; BENZYLIDENE DIMETHOXYDIMETHYLINDANONE

Bass Pro Shops Mineral Sun Stick Sunscreen Broad Spec SPF 40

Active ingredients

Titanium Dioxide 8.1%.

Zinc Oxide 6%

Purpose

Sunscreen

Uses

• Helps prevent sunburn • If used as directed with other sun protection measures (see), decreases the risk of skin cancer and early skin aging caused by the sun. Directions

Warnings

For external use only

Do not use

on damaged or broken skin

Stop use and ask a doctor

if rash occurs

When using this product

keep out of eyes. Rinse with water to remove.

Keep out of reach of children.

If swallowed, get medical help or contact a Poison Control Center right away.

Directions

• Apply liberally 15 minutes before sun exposure • • after 80 minutes of swimming or sweating • immediately after towel drying • at least every 2 hours • Children under 6 months: Ask a doctor • Spending time in the sun increases your risk of skin cancer and early skin aging. To decrease the risk, regularly use a sunscreen with Broad Spectrum SPF of 15 or higher and other sun protection measures including: • Limit time in the sun, especially from 10a.m. - 2p.m. • Wear long-sleeved shirts, pants, hats and sunglasses
Reapply: Sun Protection Measures:

Other Information

• Protect the product in this container from excessive heat and direct sunlight • May stain some fabrics • You may report serious adverse reactions to: Report Reaction, LLC., PO Box 22, Plainsboro, NJ 08536-0222 Rub in well.

Inactive Ingredients

Polyethylene, Dimethicone, Butyloctyl Salicylate, Petrolatum, Butyrospermum Parkii (Shea) Butter, C12-15 Alkyl Benzoate, Caprylic/Capric Triglyceride, Methyl Dihydroabietate, Acrylates/ Ethylhexyl Acrylate/Dimethicone Methacrylate Copolymer, Octyldodecanol, Tetrahexyldecyl Ascorbate (Vitamin C), Tocopherol (Vitamin E), Behenyl Olivate, Aluminum Hydroxide, Stearic Acid, Sorbitan Sesquioleate, Glyceryl Isostearate, Polyhydroxystearic Acid, Citric Acid, Benzylidene Dimethoxydimethylindanone.